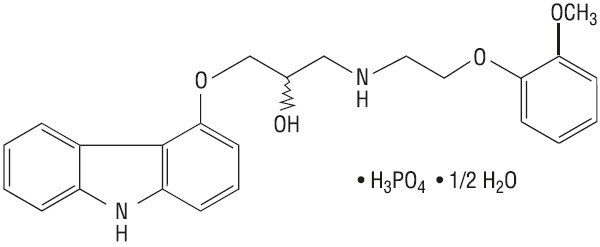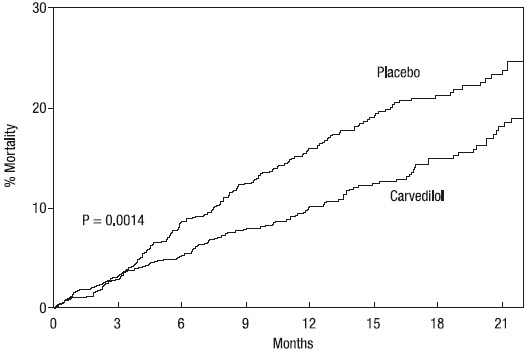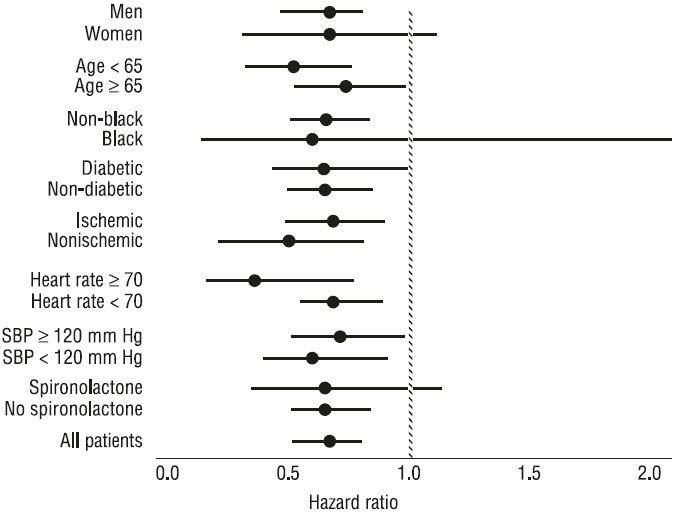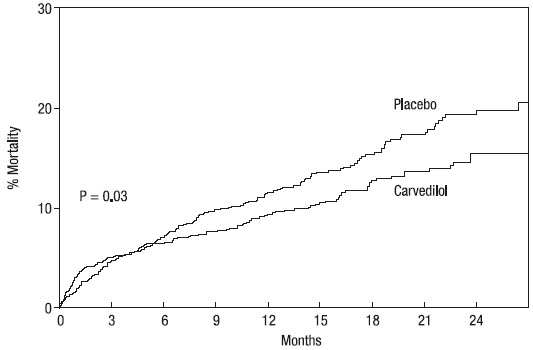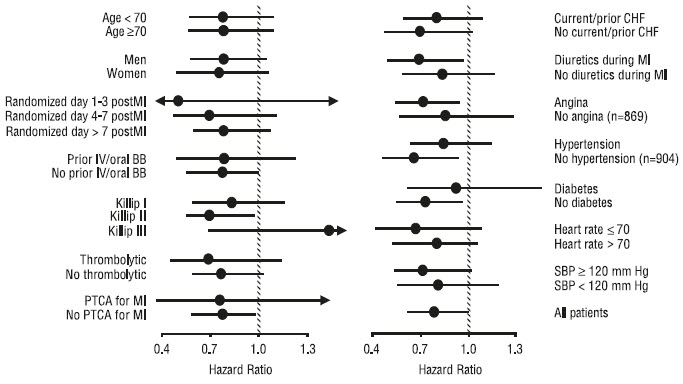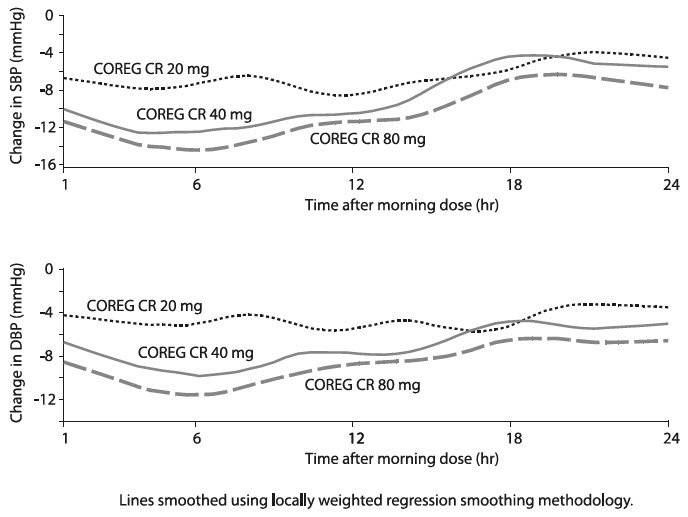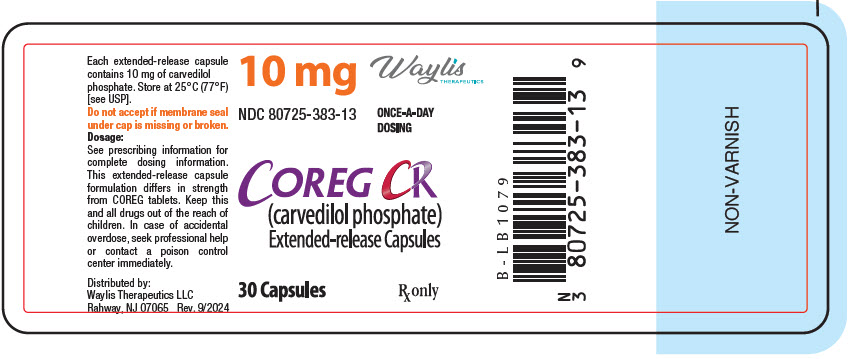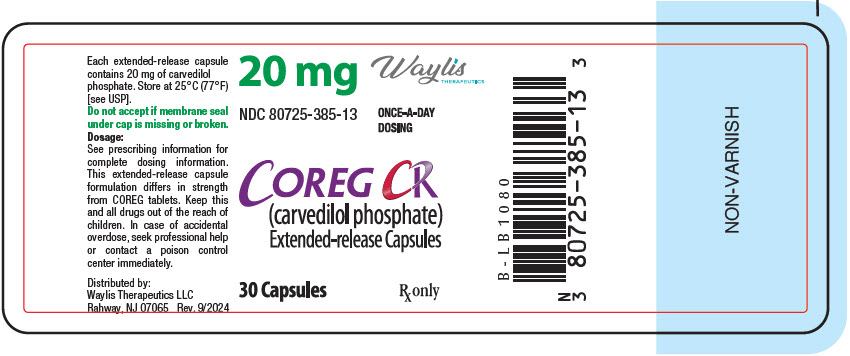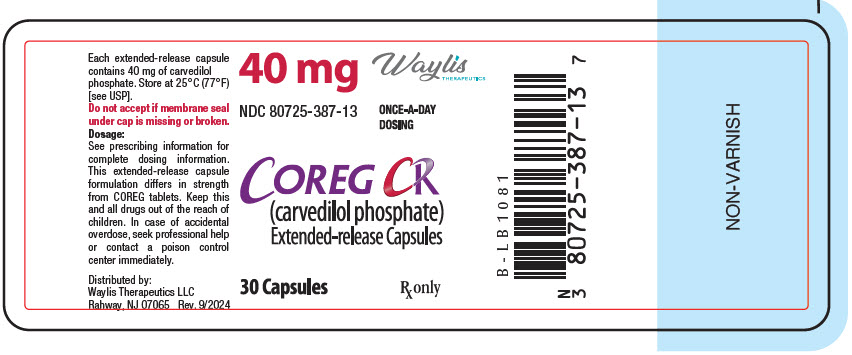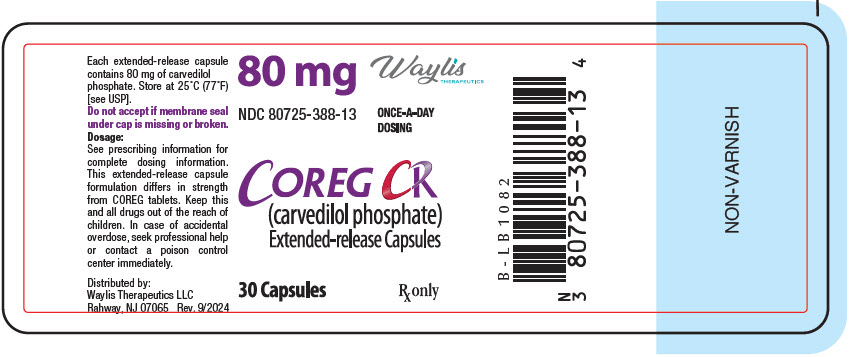 DRUG LABEL: Coreg CR
NDC: 80725-383 | Form: CAPSULE, EXTENDED RELEASE
Manufacturer: Waylis Therapeutics LLC
Category: prescription | Type: HUMAN PRESCRIPTION DRUG LABEL
Date: 20250425

ACTIVE INGREDIENTS: carvedilol phosphate 10 mg/1 1
INACTIVE INGREDIENTS: CROSPOVIDONE (120 .MU.M); HYDROGENATED CASTOR OIL; MAGNESIUM STEARATE; MICROCRYSTALLINE CELLULOSE; POVIDONE, UNSPECIFIED

HIGHLIGHTS OF PRESCRIBING INFORMATION

These highlights do not include all the information needed to use COREG CR safely and effectively. See full prescribing information for COREG CR.
COREG CR (carvedilol phosphate) extended-release capsules for oral use
Initial U.S. Approval: 1995

1 INDICATIONS AND USAGE

COREG CR is an alpha-/beta-adrenergic blocking agent indicated for the treatment of:

- mild to severe chronic heart failure. (1.1)
- left ventricular dysfunction following myocardial infarction in clinically stable patients. (1.2)
- hypertension. (1.3)

2 DOSAGE AND ADMINISTRATION

Take with food. Do not crush or chew capsules. Individualize dosage and monitor during up-titration. (2)

- Heart failure: Start at 10 mg once daily and increase to 20, 40, and then 80 mg once daily over intervals of at least 2 weeks. Maintain lower doses if higher doses are not tolerated. (2.1)
- Left ventricular dysfunction following myocardial infarction.. Start at 20 mg once daily and increase to 40 mg then 80 mg once daily after intervals of 3 to 10 days. A lower starting dose or slower titration may be used. (2.2)
- Hypertension: Start at 20 mg once daily and increase if needed for blood pressure control to 40 mg then 80 mg once daily over intervals of 1 to 2 weeks. (2.3)
- Elderly patients (>65 years of age): When switching from higher doses of immediate-release carvedilol to COREG CR, a lower starting dose should be considered to reduce the risk of hypotension and syncope. (2.5)

3 DOSAGE FORMS AND STRENGTHS

Capsules: 10 mg, 20 mg, 40 mg, 80 mg (3)

4 CONTRAINDICATIONS

- Bronchial asthma or related bronchospastic conditions. (4)
- Second- or third-degree AV block. (4)
- Sick sinus syndrome. (4)
- Severe bradycardia (unless permanent pacemaker in place). (4)
- Patients in cardiogenic shock or decompensated heart failure requiring the use of IV inotropic therapy. (4)
- Severe hepatic impairment. (2.4, 4)
- History of serious hypersensitivity reaction (e.g., Stevens-Johnson syndrome, anaphylactic reaction, angioedema) to carvedilol or any of the components of COREG CR. (4)

5 WARNINGS AND PRECAUTIONS

- Acute exacerbation of coronary artery disease upon cessation of therapy: Do not abruptly discontinue. (5.1)
- Bradycardia, hypotension, worsening heart failure/fluid retention may occur. Reduce the dose as needed. (5.2, 5.3, 5.4)
- Non-allergic bronchospasm (e.g., chronic bronchitis and emphysema): Avoid β-blockers. (4) However, if deemed necessary, use with caution and at lowest effective dose. (5.5)
- Diabetes: May mask symptoms of hypoglycemia and alter glucose levels; monitor.(5.6)

6 ADVERSE REACTIONS

The safety profile of COREG CR was similar to that observed for immediate-release carvedilol. Most common adverse events seen with immediate-release carvedilol (6.1):

- Heart failure and left ventricular dysfunction following myocardial infarction (≥10%): Dizziness, fatigue, hypotension, diarrhea, hyperglycemia, asthenia, bradycardia, weight increase.
- Hypertension (≥5%): Dizziness.

To report SUSPECTED ADVERSE REACTIONS, contact Waylis Therapeutics at 1-844-200-7910 or FDA at 1-800-FDA-1088 or www.fda.gov/medwatch.

7 DRUG INTERACTIONS

- CYP P450 2D6 enzyme inhibitors may increase and rifampin may decrease carvedilol levels. (7.1, 7.5)
- Hypotensive agents (e.g., reserpine, MAO inhibitors, clonidine) may increase the risk of hypotension and/or severe bradycardia. (7.2)
- Cyclosporine or digoxin levels may increase. (7.3, 7.4)
- Both digitalis glycosides and β-blockers slow atrioventricular conduction and decrease heart rate. Concomitant use can increase the risk of bradycardia. (7.4)
- Amiodarone may increase carvedilol levels resulting in further slowing of the heart rate or cardiac conduction. (7.6)
- Verapamil- or diltiazem-type calcium channel blockers may affect ECG and/or blood pressure. (7.7)
- Insulin and oral hypoglycemics action may be enhanced. (7.8)

FULL PRESCRIBING INFORMATION

1 INDICATIONS AND USAGE

1.1 Heart Failure

COREG CR is indicated for the treatment of mild-to-severe chronic heart failure of ischemic or cardiomyopathic origin, usually in addition to diuretics, ACE inhibitors, and digitalis, to increase survival and, also, to reduce the risk of hospitalization [see Drug Interactions (7.4), Clinical Studies (14.1)].

1.2 Left Ventricular Dysfunction following Myocardial Infarction

COREG CR is indicated to reduce cardiovascular mortality in clinically stable patients who have survived the acute phase of a myocardial infarction and have a left ventricular ejection fraction of less than or equal to 40% (with or without symptomatic heart failure) [see Clinical Studies (14.2)].

1.3 Hypertension

COREG CR is ındicated for the management of essential hypertension [see Clinical Studies (14.3, 14.4)]. It can be used alone or in combination with other antihypertensive agents, especially thiazide-type diuretics [see Drug Interactions (7.2)].

2 DOSAGE AND ADMINISTRATION

COREG CR is an extended-release capsule intended for once-daily administration. Patients controlled with immediate-release carvedilol tablets alone or in combination with other medications may be switched to COREG CR extended-release capsules based on the total daily doses shown in Table 1.

Table 1. Dosing Conversion
Daily Dose of Immediate-Release Carvedilol Tablets | Daily Dose of COREG CR Capsules [When switching from carvedilol 12.5 mg or 25 mg twice daily, a starting dose of COREG CR 20 mg or 40 mg once daily, respectively, may be warranted for elderly patients or those at increased risk of hypotension, dizziness, or syncope. Subsequent titration to higher doses should, as appropriate, be made after an interval of at least 2 weeks.]
6.25 mg (3.125 mg twice daily) | 10 mg once daily
12.5 mg (6.25 mg twice daily) | 20 mg once daily
25 mg (12.5 mg twice daily) | 40 mg once daily
50 mg (25 mg twice daily) | 80 mg once daily

COREG CR should be taken once daily in the morning with food. COREG CR should be swallowed as a whole capsule. COREG CR and/or its contents should not be crushed, chewed, or taken in divided doses.

Alternative Administration

The capsules may be carefully opened and the beads sprinkled over a spoonful of applesauce. The applesauce should not be warm because it could affect the modified-release properties of this formulation. The mixture of drug and applesauce should be consumed immediately in its entirety. The drug and applesauce mixture should not be stored for future use. Absorption of the beads sprinkled on other foods has not been tested.

2.1 Heart Failure

DOSAGE MUST BE INDIVIDUALIZED AND CLOSELY MONITORED BY A PHYSICIAN DURING UP-TITRATION. Prior to initiation of COREG CR, it is recommended that fluid retention be minımized. The recommended starting dose of COREG CR is 10 mg once daily for 2 weeks. Patients who tolerate a dose of 10 mg once daily may have their dose increased to 20, 40, and 80 mg over successive intervals of at least 2 weeks. Patients should be maintained on lower doses if higher doses are not tolerated.

Patients should be advised that initiation of treatment and (to a lesser extent) dosage increases may be associated with transient symptoms of dizziness or lightheadedness (and rarely syncope) within the first hour after dosing. Thus, during these periods, they should avoid situations such as driving or hazardous tasks, where symptoms could result in injury. Vasodilatory symptoms often do not require treatment, but it may be useful to separate the time of dosing of COREG CR from that of the ACE inhibitor or to reduce temporarily the dose of the ACE inhıbitor. The dose of COREG CR should not be increased until symptoms of worsening heart failure or vasodilation have been stabilized.

Fluid retention (with or without transient worsening heart failure symptoms) should be treated by an increase in the dose of diuretics.

The dose of COREG CR should be reduced if patients experience bradycardia (heart rate less than 55 beats per minute).

Episodes of dizziness or fluid retention during initiation of COREG CR can generally be managed without discontinuation of treatment and do not preclude subsequent successful titration of, or a favorable response to, COREG CR.

2.2 Left Ventricular Dysfunction following Myocardial Infarction

DOSAGE MUST BE INDIVIDUALIZED AND MONITORED DURING UP-TITRATION. Treatment with COREG CR may be started as an inpatient or outpatient and should be started after the patient is hemodynamically stable and fluid retention has been minimized. It is recommended that COREG CR be started at 20 mg once daily and increased after 3 to 10 days, based on tolerabılity, to 40 mg once daily, then again to the target dose of 80 mg once daily. A lower starting dose may be used (10 mg once daily) and/or the rate of up-titration may be slowed if clinically indicated (e.g., due to low blood pressure or heart rate, or fluid retention). Patients should be maintained on lower doses if higher doses are not tolerated. The recommended dosing regimen need not be altered in patients who received treatment with an IV or oral β-blocker during the acute phase of the myocardial infarction.

2.3 Hypertension

DOSAGE MUST BE INDIVIDUALIZED. The recommended starting dose of COREG CR is 20 mg once daily. If this dose is tolerated, using standing systolic pressure measured about 1 hour after dosing as a guide, the dose should be maintained for 7 to 14 days, and then increased to 40 mg once daily if needed, based on trough blood pressure, again using standing systolic pressure 1 hour after dosing as a guide for tolerance. This dose should also be maintained for 7 to 14 days and can then be adjusted upward to 80 mg once daily if tolerated and needed.Although not specifically studied, it is anticipated the full antihypertensive effect of COREG CR would be seen within 7 to 14 days as had been demonstrated with immediate-release carvedilol. Total daily dose should not exceed 80 mg.

Concomitant administration with a diuretic can be expected to produce additive effects and exaggerate the orthostatic component of carvedilol action.

2.4 Hepatic Impairment

COREG CR should not be given to patients with severe hepatic ımpairment [see Contraindications (4)].

2.5 Geriatric Use

When switching elderly patients (aged 65 years or older) who are taking the higher doses of immediate-release carvedilol tablets (25 mg twice daily) to COREG CR, a lower starting dose (40 mg) of COREG CR is recommended to minimize the potential for dizziness, syncope, or hypotension [see Dosage and Administration (2)]. Patients who have switched and who tolerate COREG CR should, as appropriate, have their dose increased after an interval of at least 2 weeks [see Use in Specific Populations (8.5)].

3 DOSAGE FORMS AND STRENGTHS

The hard gelatin capsules are filled with white to off-white microparticles and are available in the following strengths:

- 10 mg - white and green capsule shell printed with "GSLGK" and "10 mg"
- 20 mg - white and yellow capsule shell printed with "GSMHV" and "20 mg"
- 40 mg - yellow and green capsule shell printed with "GSETX" and "40 mg"
- 80 mg - white capsule shell printed with "GSF1L" and "80 mg"

4 CONTRAINDICATIONS

COREG CR is contraindicated in the following conditions:

- Bronchial asthma or related bronchospastic conditions. Deaths from status asthmaticus have been reported following single doses of immediate-release carvedilol.
- Second- or third-degree AV block.
- Sick sinus syndrome.
- Severe bradycardia (unless a permanent pacemaker is in place).
- Patients with cardiogenic shock or who have decompensated heart failure requiring the use of intravenous inotropic therapy. Such patients should first be weaned from intravenous therapy before initiating COREG CR.
- Patients with severe hepatic impairment.
- Patients with a history of a serious hypersensitivity reaction (e.g., Stevens-Johnson syndrome, anaphylactic reaction, angioedema) to carvedilol or any of the components of COREG CR.

5 WARNINGS AND PRECAUTIONS

In clinical trials of COREG CR in subjects with hypertension (338 subjects) and in subjects with left ventricular dysfunction following a myocardial infarction or heart failure (187 subjects), the profile of adverse events observed with carvedilol phosphate was generally similar to that observed with the administration of immediate-release carvedilol. Therefore, the information included within this section is based on data from controlled clinical trials with COREG CR as well as immediate-release carvedilol.

5.1 Cessation of Therapy

Patients with coronary artery disease, who are being treated with COREG CR, should be advised against abrupt discontinuation of therapy. Severe exacerbation of angina and the occurrence of myocardial infarction and ventricular arrhythmias have been reported in patients with angina following the abrupt discontinuation of therapy with β-blockers. The last 2 complications may occur with or without preceding exacerbation of the angina pectoris. As with other β-blockers, when discontinuation of COREG CR is planned, the patients should be carefully observed and advised to limit physical activity to a minimum. COREG CR should be discontinued over 1 to 2 weeks whenever possible. If the angina worsens or acute coronary insufficiency develops, it is recommended that COREG CR be promptly reinstituted, at least temporarily. Because coronary artery disease is common and may be unrecognized, it may be prudent not to discontinue therapy with COREG CR abruptly even in patients treated only for hypertension or heart failure.

5.2 Bradycardia

In clinical trials with immediate-release carvedilol, bradycardia was reported in about 2% of hypertensive subjects, 9% of subjects with heart failure, and 6.5% of subjects with myocardial infarction and left ventricular dysfunction. Bradycardia was reported in 0.5% of subjects receiving COREG CR in a trial of subjects with heart failure and subjects with myocardial infarction and left ventricular dysfunction. There were no reports of bradycardia in the clinical trial of COREG CR in hypertension. However, if pulse rate drops below 55 beats per minute, the dosage of COREG CR should be reduced.

5.3 Hypotension

In clinical trials of primarily mild-to-moderate heart failure with immediate-release carvedilol, hypotension and postural hypotension occurred in 9.7% and syncope in 3.4% of subjects receiving carvedilol compared with 3.6% and 2.5% of placebo subjects, respectively. The risk for these events was highest during the first 30 days of dosing, corresponding to the up-titration period and was a cause for discontinuation of therapy in 0.7% of carvedilol subjects, compared with 0.4% of placebo subjects. In a long-term, placebo-controlled trial in severe heart failure (COPERNICUS), hypotension and postural hypotension occurred in 15.1% and syncope in 2.9% of subjects with heart failure receiving carvedilol compared with 8.7% and 2.3% of placebo subjects, respectively. These events were a cause for discontinuation of therapy in 1.1% of carvedilol subjects, compared with 0.8% of placebo subjects.

In a trial comparing subjects with heart failure switched to COREG CR or maintained on immediate-release carvedilol, there was a 2-fold increase in the combined incidence of hypotension, syncope, or dizziness in elderly subjects (older than 65 years) switched from the highest dose of carvedilol (25 mg twice daily) to COREG CR 80 mg once daily [see Dosage and Administration (2), Use in Specific Populations (8.5)].

In the clinical trial of COREG CR in hypertensive subjects, syncope was reported in 0.3% of subjects receivıng COREG CR compared with 0% of subjects receiving placebo. There were no reports of postural hypotension in this trial. Postural hypotension occurred in 1.8% and syncope in 0.1% of hypertensive subjects receiving immediate-release carvedilol, primarily following the initial dose or at the time of dose increase and was a cause for discontinuation of therapy in 1% of subjects.

In the CAPRICORN trial of survivors of an acute myocardial infarction with left ventricular dysfunction, hypotension or postural hypotension occurred in 20.2% of subjects receiving carvedilol compared with 12.6% of placebo subjects. Syncope was reported in 3.9% and 1.9% of subjects, respectively. These events were a cause for discontinuation of therapy in 2.5% of subjects receiving carvedilol, compared with 0.2% of placebo subjects.

Starting with a low dose, administration with food, and gradual up-titration should decrease the likelihood of syncope or excessive hypotension [see Dosage and Administration (2.1, 2.2, 2.3)]. During initiation of therapy, the patient should be cautioned to avoid situations such as driving or hazardous tasks, where injury could result should syncope occur.

5.4 Heart Failure/Fluid Retention

Worsening heart failure or fluid retention may occur during up-titration of carvedilol. If such symptoms occur, diuretics should be increased, and the dose of COREG CR should not be advanced until clinical stability resumes [see Dosage and Administration (2)]. Occasionally it is necessary to lower the dose of COREG CR or temporarily discontinue it. Such episodes do not preclude subsequent successful titration of, or a favorable response to, COREG CR. In a placebo -controlled trial of subjects with severe heart failure, worsening heart failure during the first 3 months was reported to a similar degree with immediate-release carvedilol and with placebo. When treatment was maintained beyond 3 months, worsening heart failure was reported less frequently in subjects treated with carvedilol than with placebo. Worsening heart failure observed during long-term therapy is more likely to be related to the patients' underlying disease than to treatment with carvedilol.

5.5 Non-allergic Bronchospasm

Patients with bronchospastic disease (e.g., chronic bronchitis, emphysema) should, in general, not receive β-blockers. COREG CR may be used with caution, however, in patients who do not respond to, or cannot tolerate, other antihypertensive agents. It is prudent, if COREG CR is used, to use the smallest effective dose, so that inhibition of endogenous or exogenous β-agonists is minimized.

In clinical trials of subjects with heart failure, subjects with bronchospastic disease were enrolled if they did not require oral or inhaled medication to treat their bronchospastic disease. In such patients, it is recommended that COREG CR be used with caution. The dosing recommendations should be followed closely, and the dose should be lowered if any evidence of bronchospasm is observed during up-titration.

5.6 Effects on Blood Sugar

Betablockers may prevent early warning signs of hypoglycemia, such as tachycardia, and increase the risk for severe or prolonged hypoglycemia at any time during treatment, especially in patients with diabetes mellitus or children and patients who are fasting (i.e., surgery, not eating regularly, or are vomiting). If severe hypoglycemia occurs, patients should be instructed to seek emergency treatment.

In patients with heart failure and diabetes, carvedilol therapy may lead to worsening hyperglycemia, which responds to intensification of hypoglycemic therapy. It is recommended that blood glucose be monitored when dosing with COREG CR is initiated, adjusted, or discontinued. Trials designed to examine the effects of carvedilol on glycemic control in patients with diabetes and heart failure have not been conducted.

In a trial designed to examine the effects of immediate-release carvedilol on glycemic control in a population with mild-to-moderate hypertension and well-controlled type 2 diabetes mellitus, carvedilol had no adverse effect on glycemic control, based on HbA1c measurements [see Clinical Studies (14.4)].

5.7 Peripheral Vascular Disease

β-blockers can precipitate or aggravate symptoms of arterial insufficiency in patients with peripheral vascular disease. Caution should be exercised in such individuals.

5.8 Deterioration of Renal Function

Rarely, use of carvedilol in patients with heart failure has resulted in deterioration of renal function. Patients at risk appear to be those with low blood pressure (systolic blood pressure less than 100 mm Hg), ischemic heart disease and diffuse vascular disease, and/or underlying renal insufficiency. Renal function has returned to baseline when carvedilol was stopped. In patients with these risk factors, it is recommended that renal function be monitored during up-titration of COREG CR and the drug discontinued or dosage reduced if worsening of renal function occurs.

5.9 Major Surgery

Chronically administered β-blocking therapy should not be routinely withdrawn prior to major surgery; however, the impaired ability of the heart to respond to reflex adrenergic stimuli may augment the risks of general anesthesia and surgical procedures.

5.10 Thyrotoxicosis

β-adrenergic blockade may mask clinical signs of hyperthyroidism, such as tachycardia. Abrupt withdrawal of β-blockade may be followed by an exacerbation of the symptoms of hyperthyroidism or may precipitate thyroid storm.

5.11 Pheochromocytoma

In patients with pheochromocytoma, an α-blocking agent should be initiated prior to the use of any β-blocking agent. Although carvedilol has both α- and β-blocking pharmacologic activities, there has been no experience with its use in this condition. Therefore, caution should be taken in the administration of carvedilol to patients suspected of having pheochromocytoma.

5.12 Prinzmetal's Variant Angina

Agents with non-selective β-blocking activity may provoke chest pain in patients with Prinzmetal's variant angina. There has been no clinical experience with carvedilol in these patients although the α-blocking activity may prevent such symptoms. However, caution should be taken in the administration of COREG CR to patients suspected of having Prinzmetal's variant angina.

5.13 Risk of Anaphylactic Reaction

While taking β-blockers, patients with a history of severe anaphylactic reaction to a variety of allergens may be more reactive to repeated challenge, either accidental, diagnostic, or therapeutic. Such patients may be unresponsive to the usual doses of epinephrine used to treat allergic reaction.

5.14 Intraoperative Floppy Iris Syndrome

Intraoperative Floppy Iris Syndrome (IFIS) has been observed during cataract surgery in some patients treated with alpha-1 blockers (COREG CR is an alpha/beta blocker). This variant of small pupil syndrome is characterized by the combination of a flaccid iris that billows in response to intraoperative irrigation currents, progressive intraoperative miosis despite preoperative dilation with standard mydriatic drugs, and potential prolapse of the iris toward the phacoemulsification incisions. The patient's ophthalmologist should be prepared for possible modifications to the surgical technique, such as utilization of iris hooks, iris dilator rings, or viscoelastic substances. There does not appear to be a benefit of stopping alpha-1 blocker therapy prior to cataract surgery.

6 ADVERSE REACTIONS

6.1 Clinical Trials Experience

Because clinical trials are conducted under widely varying conditions, adverse reaction rates observed in the clinical trials of a drug cannot be directly compared with rates in the clinical trials of another drug and may not reflect the rates observed in practice.

Carvedilol has been evaluated for safety in subjects with heart failure (mild, moderate, and severe), in subjects with left ventricular dysfunction following myocardial infarction, and in hypertensive subjects. The observed adverse event profile was consistent with the pharmacology of the drug and the health status of the subjects in the clinical trials. Adverse events reported for each of these populations reflecting the use of either COREG CR or immediate-release carvedilol are provided below. Excluded are adverse events considered too general to be informative, and those not reasonably associated with the use of the drug because they were associated with the condition being treated or are very common in the treated population. Rates of adverse events were generally similar across demographic subsets (men and women, elderly and non-elderly, blacks and non-blacks). COREG CR has been evaluated for safety in a 4-week (2 weeks of immediate-release carvedilol and 2 weeks of COREG CR) clinical trial (n = 187) which included 157 subjects with stable mild, moderate, or severe chronic heart failure and 30 subjects with left ventricular dysfunction following acute myocardial infarction.The profile of adverse events observed with COREG CR in this small, short-term trial was generally similar to that observed with immediate-release carvedilol. Differences in safety would not be expected based on the similarity in plasma levels for COREG CR and immediate-release carvedilol.

Heart Failure

The following information describes the safety experience in heart failure with immediate-release carvedilol.

Carvedilol has been evaluated for safety in heart failure in more than 4,500 subjects worldwide of whom more than 2,100 participated in placebo-controlled clinical trials. Approximately 60% of the total treated population in placebo-controlled clinıcal trials received carvedilol for at least 6 months and 30% received carvedilol for at least 12 months. In the COMET trial, 1,511 subjects with mild-to-moderate heart failure were treated with carvedilol for up to 5.9 years (mean: 4.8 years). Both in U.S. clinical trials in mild-to-moderate heart failure that compared carvedilol in daily doses up to 100 mg (n = 765) with placebo (n = 437), and in a multinational clinical trial in severe heart failure (COPERNICUS) that compared carvedilol in daily doses up to 50 mg (n = 1,156) with placebo (n = 1,133), discontinuation rates for adverse experiences were similar in carvedilol and placebo subjects. In placebo-controlled clinical trials, the only cause of discontinuation greater than 1% and occurring more often on carvedilol was dizziness (1.3% on carvedilol, 0.6% on placebo in the COPERNICUS trial).

Table 2 shows adverse events reported in subjects with mild-to-moderate heart failure enrolled in U.S. placebo-controlled clinical trials, and with severe heart failure enrolled in the COPERNICUS trial. Shown are adverse events that occurred more frequently in drug-treated subjects than placebo-treated subjects with an incidence of greater than 3% in subjects treated with carvedilol regardless of causality. Median trial medication exposure was 6.3 months for both carvedilol and placebo subjects in the trials of mild-to-moderate heart failure and 10.4 months in the trial of subjects with severe heart failure. The adverse event profile of carvedilol observed in the long-term COMET trial was generally similar to that observed in the U.S. Heart Failure Trials.

Table 2. Adverse Events (%) Occurring More Frequently with Immediate-Release Carvedilol than with Placebo in Subjects with Mild-to-Moderate Heart Failure (HF) Enrolled in U.S. Heart Failure Trials or in Subjects with Severe Heart Failure in the COPERNICUS Trial (Incidence >3% in Subjects Treated with Carvedilol, Regardless of Causality)
Body System/Adverse Event | Mild-to-Moderate HF |  | Severe HF
Body System/Adverse Event | Carvedilol | Placebo | Carvedilol | Placebo
Body System/Adverse Event | (n = 765) | (n = 437) | (n = 1,156) | (n = 1,133)
Body as a Whole
Asthenia | 7 | 7 | 11 | 9
Fatigue | 24 | 22 | — | —
Digoxin level increased | 5 | 4 | 2 | 1
Edema generalized | 5 | 3 | 6 | 5
Edema dependent | 4 | 2 | — | —
Cardiovascular
Bradycardia | 9 | 1 | 10 | 3
Hypotension | 9 | 3 | 14 | 8
Syncope | 3 | 3 | 8 | 5
Angina pectoris | 2 | 3 | 6 | 4
Central Nervous System
Dizziness | 32 | 19 | 24 | 17
Headache | 8 | 7 | 5 | 3
Gastrointestinal
Diarrhea | 12 | 6 | 5 | 3
Nausea | 9 | 5 | 4 | 3
Vomiting | 6 | 4 | 1 | 2
Metabolic
Hyperglycemia | 12 | 8 | 5 | 3
Weight increase | 10 | 7 | 12 | 11
BUN increased | 6 | 5 | — | —
NPN increased | 6 | 5 | — | —
Hypercholesterolemia | 4 | 3 | 1 | 1
Edema peripheral | 2 | 1 | 7 | 6
Musculoskeletal
Arthralgia | 6 | 5 | 1 | 1
Respiratory
Cough increased | 8 | 9 | 5 | 4
Rales | 4 | 4 | 4 | 2
Vision
Vision abnormal | 5 | 2 | — | —

Cardiac failure and dyspnea were also reported in these trials, but the rates were equal or greater in subjects who received placebo.

The following adverse events were reported with a frequency of greater than 1% but less than or equal to 3% and more frequently with carvedilol in either the U.S. placebo-controlled trials in subjects with mild-to-moderate heart failure or in subjects with severe heart failure in the COPERNICUS trial.

Incidence greater than 1% to less than or equal to 3%

Body as a Whole: Allergy, malaise, hypovolemia, fever, leg edema.

Cardiovascular: Fluid overload, postural hypotension, aggravated angina pectoris, AV block, palpitation, hypertension.

Central and Peripheral Nervous System: Hypesthesia, vertigo, paresthesia.

Gastrointestinal: Melena, periodontitis.

Liver and Biliary System: SGPT increased, SGOT increased.

Metabolic and Nutritional: Hyperuricemia, hypoglycemia, hyponatremia, increased alkaline phosphatase, glycosuria, hypervolemia, diabetes mellitus, GGT increased, weight loss, hyperkalemia, creatinine increased.

Musculoskeletal: Muscle cramps.

Platelet, Bleeding, and Clotting: Prothrombin decreased, purpura, thrombocytopenia.

Psychiatric: Somnolence.

Reproductive, male: Impotence.

Special Senses: Blurred vision.

Urinary System: Renal insufficiency, albuminuria, hematuria.

Left Ventricular Dysfunction following Myocardial Infarction

The following information describes the safety experience in left ventricular dysfunction following acute myocardial infarction with immediate-release carvedilol.

Carvedilol has been evaluated for safety in survivors of an acute myocardial infarction with left ventricular dysfunction in the CAPRICORN trial which involved 969 subjects who received carvedilol and 980 who received placebo. Approximately 75% of the subjects received carvedilol for at least 6 months and 53% received carvedilol for at least 12 months. Subjects were treated for an average of 12.9 months and 12.8 months with carvedilol and placebo, respectively.

The most common adverse events reported with carvedilol in the CAPRICORN trial were consistent with the profile of the drug in the U.S. heart failure trials and the COPERNICUS trial. The only additional adverse events reported in CAPRICORN in greater than 3% of the subjects and more commonly on carvedilol were dyspnea, anemia, and lung edema. The following adverse events were reported with a frequency of > 1% but ≤ 3% and more frequently with carvedilol: flu syndrome, cerebrovascular accident, peripheral vascular disorder, hypotonia, depression, gastrointestinal pain, arthritis, and gout. The overall rates of discontinuations due to adverse events were similar in both groups of subjects. In this database, the only cause of discontinuation > 1% and occurring more often on carvedilol was hypotension (1.5% on carvedilol, 0.2% on placebo).

Hypertension

COREG CR was evaluated for safety in an 8-week double-blind trial in 337 subjects with essential hypertension. The profile of adverse events observed with COREG CR was generally simılar to that observed with immediate-release carvedilol. The overall rates of discontinuations due to adverse events were similar between COREG CR and placebo.

Table 3. Adverse Events (%) Occurring More Frequently with COREG CR than with Placebo in Subjects with Hypertension (Incidence ≥1% in Subjects Treated with Carvedilol, Regardless of Causality)
Adverse Event | COREG CR (n = 253) | Placebo (n = 84)
Nasopharyngitis | 4 | 0
Dizziness | 2 | 1
Nausea | 2 | 0
Edema peripheral | 2 | 1
Nasal congestion | 1 | 0
Paresthesia | 1 | 0
Sinus congestion | 1 | 0
Diarrhea | 1 | 0
Insomnia | 1 | 0

The following information describes the safety experience in hypertension with immediate-release carvedilol.

Carvedilol has been evaluated for safety in hypertension in more than 2,193 subjects in U.S. clinical trials and in 2,976 subjects in international clinical trials. Approximately 36% of the total treated population received carvedilol for at least 6 months. In general, carvedilol was well tolerated at doses up to 50 mg daily. Most adverse events reported during carvedilol therapy were of mild to moderate severity. In U.S. controlled clinical trials directly comparing carvedilol monotherapy in doses up to 50 mg (n = 1,142) with placebo (n = 462), 4.9% of carvedilol subjects discontinued for adverse events versus 5.2% of placebo subjects. Although there was no overall difference in discontinuation rates, discontinuations were more common in the carvedilol group for postural hypotension (1% versus 0). The overall incidence of adverse events in U.S. placebo-controlled trials was found to increase with increasing dose of carvedilol. For individual adverse events this could only be distinguished for dizziness, which increased in frequency from 2% to 5% as total daily dose increased from 6.25 mg to 50 mg as single or divıded doses.

Table 4 shows adverse events in U.S. placebo-controlled clinical trials for hypertension that occurred with an incidence of greater than or equal to 1% regardless of causality and that were more frequent in drug-treated subjects than placebo-treated subjects.

Table 4. Adverse Events (% Occurrence) in U.S. Placebo-Controlled Hypertension Trials with Immediate-Release Carvedilol (Incidence ≥1% in Subjects Treated with Carvedilol, Regardless of Causality) [Shown are events with rate >1% rounded to nearest integer.]
Adverse Event | Carvedilol (n = 1,142) | Placebo (n = 462)
Cardiovascular
Bradycardia | 2 | —
Postural hypotension | 2 | —
Peripheral edema | 1 | —
Central Nervous System
Dizziness | 6 | 5
Insomnia | 2 | 1
Gastrointestinal
Diarrhea | 2 | 1
Hematologic
Thrombocytopenia | 1 | —
Metabolic
Hypertriglyceridemia | 1 | —

Dyspnea and fatigue were also reported in these trials, but the rates were equal or greater in subjects who received placebo.

The following adverse events not described above were reported as possibly or probably related to carvedilol in worldwide open or controlled trials with carvedilol in subjects with hypertension or heart failure.

Incidence greater than 0.1% to less than or equal to 1%

Cardiovascular: Peripheral ischemia, tachycardia.

Central and Peripheral Nervous System: Hypokinesia.

Gastrointestinal: Bilirubinemia, increased hepatic enzymes (0.2% of hypertension patients and 0.4% of heart failure patients were discontinued from therapy because of increases in hepatic enzymes) [see Adverse Reactions (6.2)].

Psychiatric: Nervousness, sleep disorder, aggravated depression, impaired concentration, abnormal thinking, paranoia, emotional lability.

Respiratory System: Asthma [see Contraindications (4)].

Reproductive, male: Decreased libido.

Skin and Appendages: Pruritus, rash erythematous, rash maculopapular, rash psoriaform, photosensitivity reaction.

Special Senses: Tinnitus.

Urinary System: Micturition frequency increased.

Autonomic Nervous System: Dry mouth, sweating increased.

Metabolic and Nutritional: Hypokalemia, hypertriglyceridemia.

Hematologic: Anemia, leukopenia.

The following events were reported in less than or equal to 0.1% of subjects and are potentially important: complete AV block, bundle branch block, myocardial ischemia, cerebrovascular disorder, convulsions, migraine, neuralgia, paresis, anaphylactoid reaction, alopecia, exfoliative dermatitis, amnesia, GI hemorrhage, bronchospasm, pulmonary edema, decreased hearing, respiratory alkalosis, increased BUN, decreased HDL, pancytopenia, and atypical lymphocytes.

Laboratory Abnormalities

Reversible elevations in serum transaminases (ALT or AST) have been observed during treatment with carvedilol. Rates of transaminase elevations (2- to 3- times the upper limit of normal) observed during controlled clinical trials have generally been similar between subjects treated with carvedilol and those treated with placebo. However, transaminase elevations, confirmed by rechallenge, have been observed with carvedilol. In a long-term, placebo-controlled trial in severe heart failure, subjects treated with carvedilol had lower values for hepatic transaminases than subjects treated with placebo, possibly because carvedilol-induced improvements in cardiac function led to less hepatic congestion and/or improved hepatic blood flow.

Carvedilol therapy has not been associated with clinically significant changes in serum potassium, total triglycerides, total cholesterol, HDL cholesterol, uric acid, blood urea nitrogen, or creatinine. No clinically relevant changes were noted in fasting serum glucose in hypertensive subjects; fasting serum glucose was not evaluated in the heart failure clinical trials.

6.2 Postmarketing Experience

The following adverse reactions have been identified during post-approval use of COREG or COREG CR. Because these reactions are reported voluntarily from a population of uncertain size, it is not always possible to reliably estimate their frequency or establish a causal relationship to drug exposure.

Blood and Lymphatic System Disorders

Aplastic anemia.

Immune System Disorders

Hypersensitivity (e.g., anaphylactic reactions, angioedema, urticaria).

Renal and Urinary Disorders

Urinary incontinence.

Respiratory, Thoracic, and Mediastinal Disorders

Interstitial pneumonitis.

Skin and Subcutaneous Tissue Disorders

Stevens-Johnson syndrome, toxic epidermal necrolysis, erythema multiforme.

7 DRUG INTERACTIONS

7.1 CYP2D6 Inhibitors and Poor Metabolizers

Interactions of carvedilol with potent inhibitors of CYP2D6 isoenzyme (such as quinidine, fluoxetine, paroxetine, and propafenone) have not been studied, but these drugs would be expected to increase blood levels of the R(+) enantiomer of carvedilol [see Clinical Pharmacology (12.3)]. Retrospective analysis of side effects in clinical trials showed that poor 2D6 metabolizers had a higher rate of dizziness during up-titration, presumably resulting from vasodilating effects of the higher concentrations of the α-blocking R(+) enantiomer.

7.2 Hypotensive Agents

Patients taking a β-blocker and a drug that can deplete catecholamines (e.g., reserpine and monoamine oxidase inhibitors) should be observed closely for signs of hypotension and/or severe bradycardia.

Concomitant administration of clonidine with a β-blocker may cause hypotension and bradycardia. When concomitant treatment with a β-blocker and clonidine is to be terminated, the β-blocker should be discontinued first. Clonidine therapy can then be discontinued several days later by gradually decreasing the dosage.

7.3 Cyclosporine

Modest increases in mean trough cyclosporine concentrations were observed following initiation of carvedilol treatment in 21 renal transplant subjects suffering from chronic vascular rejection. In about 30% of subjects, the dose of cyclosporine had to be reduced in order to maintain cyclosporine concentrations within the therapeutic range, while in the remainder no adjustment was needed. On the average for the group, the dose of cyclosporine was reduced about 20% in these subjects. Due to wide interindividual variability in the dose adjustment required, it is recommended that cyclosporine concentrations be monitored closely after initiation of carvedilol therapy and that the dose of cyclosporine be adjusted as appropriate.

7.4 Digitalis Glycosides

Both digitalis glycosides and β-blockers slow atrioventricular conduction and decrease heart rate. Concomitant use can increase the risk of bradycardia. Digoxin concentrations are increased by about 15% when digoxin and carvedilol are administered concomitantly. Therefore, increased monitoring of digoxin is recommended when initiating, adjusting, or discontinuing COREG CR [see Drug-Drug Interactions (12.5)].

7.5 Inducers/Inhibitors of Hepatic Metabolism

Rifampin reduced plasma concentrations of carvedilol by about 70% [see Drug-Drug Interactions (12.5)]. Cimetidine increased area under the curve (AUC) by about 30% but caused no change in Cmax [see Drug-Drug Interactions (12.5)].

7.6 Amiodarone

Amiodarone and its metabolite desethyl amiodarone, inhibitors of CYP2C9, and P-glycoprotein increased concentrations of the S(-) enantiomer of carvedilol by at least 2-fold [see Drug-Drug Interactions (12.5)]. The concomitant administration of amiodarone or other CYP2C9 inhibitors such as fluconazole with COREG CR may enhance the β-blocking activity, resulting in further slowing of the heart rate or cardiac conduction. Patients should be observed for signs of bradycardia or heart block, particularly when one agent is added to pre-existing treatment with the other.

7.7 Calcium Channel Blockers

Conduction disturbance (rarely with hemodynamic compromise) has been observed when COREG CR is coadministered with diltiazem. As with other β-blockers, if COREG CR is administered with calcium channel blockers of the verapamil or diltiazem type, it is recommended that ECG and blood pressure be monitored.

7.8 Insulin or Oral Hypoglycemics

β-blockers properties may enhance the blood-sugar-reducing effect of insulin and oral hypoglycemics. Therefore, in patients taking insulin or oral hypoglycemics, regular monitoring of blood glucose is recommended [see Warnings and Precautions (5.6)].

7.9 Proton Pump Inhibitors

There is no clinically meaningful increase in AUC and Cmax with concomitant administration of carvedilol extended-release capsules with pantoprazole.

7.10 Anesthesia

If treatment with COREG CR is to be continued perioperatively, particular care should be taken when anesthetic agents that depress myocardial function, such as ether, cyclopropane, and trichloroethylene, are used [see Overdosage (10)].

8 USE IN SPECIFIC POPULATIONS

8.1 Pregnancy

Risk Summary

Available data regarding use of COREG CR in pregnant women are insufficient to determine whether there are drug-associated risks of adverse developmental outcomes. There are risks to the mother and fetus associated with poorly controlled hypertension in pregnancy. The use of beta blockers during the third trimester of pregnancy may increase the risk of hypotension, bradycardia, hypoglycemia, and respiratory depression in the neonate (see Clinical Considerations). In animal reproduction studies, there was no evidence of adverse developmental outcomes at clinically relevant doses (see Data). Oral administration of carvedilol to pregnant rats during organogenesis resulted in post-implantation loss, decreased fetal body weight, and an increased frequency of delayed fetal skeletal development at maternally toxic doses that were 50 times the maximum recommended human dose (MRHD). In addition, oral administration of carvedilol to pregnant rabbits during organogenesis resulted in increased post-implantation loss at doses 25 times the MRHD (see Data).

The estimated background risk of major birth defects and miscarriage for the indicated populations are unknown. All pregnancies have a background risk of birth defect, loss, or other adverse outcomes. In the U.S. general population, the estimated background risk of major birth defects and miscarriage in clinically recognized pregnancies is 2% to 4% and 15% to 20%, respectively.

Clinical Considerations

Disease-Associated Maternal and/or Embryo/Fetal Risk: Hypertension in pregnancy increases the maternal risk for preeclampsia, gestational diabetes, premature delivery, and delivery complications (e.g., need for cesarean section and post-partum hemorrhage). Hypertension increases the fetal risk for intrauterine growth restriction and intrauterine death. Pregnant women with hypertension should be carefully monitored and managed accordingly.

Fetal/Neonatal Adverse Reactions: Neonates of women with hypertension who are treated with beta-blockers during the third trimester of pregnancy may be at increased risk for hypotension, bradycardia, hypoglycemia, and respiratory depression. Observe newborns for symptoms of hypotension, bradycardia, hypoglycemia, and respiratory depression and manage accordingly.

Data

Animal Data: Studies performed in rats and rabbits given carvedilol during fetal organogenesis revealed increased post-implantation loss in rats at a maternally toxic dose of 300 mg per kg per day (50 times the MRHD as mg per m^2) and in rabbits (in the absence of maternal toxicity) at doses of 75 mg per kg per day (25 times the MRHD as mg per m^2). In the rats, there was also a decrease in fetal body weight at 300 mg per kg per day (50 times the MRHD as mg per m^2) accompanied by an increased incidence of fetuses with delayed skeletal development. In rats, the no-effect level for embryo-fetal toxicity was 60 mg per kg per day (10 times the MRHD as mg per m^2); in rabbits, it was 15 mg per kg per day (5 times the MRHD as mg per m^2). In a pre-and post-natal development study in rats administered carvedilol from late gestation through lactation, increased embryo-lethality was observed at a maternally toxic dose of 200 mg per kg per day (approximately 32 times the MRHD as mg per m^2), and pup mortality and delays in physical growth/development were observed at 60 mg per kg per day (10 times the MRHD as mg per m^2) in the absence of maternal toxicity. The no-effect level was 12 mg per kg per day (2 times the MRHD as mg per m2). Carvedilol was present in fetal rat tissue.

8.2 Lactation

Risk Summary

There are no data on the presence of carvedilol in human milk, the effects on the breastfed infant, or the effects on milk production. Carvedilol is present in the milk of lactating rats. The developmental and health benefits of breastfeeding should be considered along with the mother's clinical need for COREG CR and any potential adverse effects on the breastfed infant from COREG CR or from the underlying maternal condition.

8.4 Pediatric Use

Effectiveness of carvedilol in patients younger than 18 years has not been established.

In a double-blind trial, 161 children (mean age: 6 years; range: 2 months to 17 years; 45% younger than 2 years) with chronic heart failure [NYHA class II-IV, left ventricular ejection fraction less than 40% for children with a systemic left ventricle (LV), and moderate-severe ventricular dysfunction qualitatively by echo for those with a systemic ventricle that was not an LV] who were receiving standard background treatment were randomized to placebo or to 2 dose levels of carvedilol. These dose levels produced placebo-corrected heart rate reduction of 4 to 6 heart beats per minute, indicative of β-blockade activity. Exposure appeared to be lower in pediatric subjects than adults. After 8 months of follow-up, there was no significant effect of treatment on clinical outcomes. Adverse reactions in this trial that occurred in greater than 10% of subjects treated with immediate-release carvedilol and at twice the rate of placebo-treated subjects included chest pain (17% versus 6%), dizziness (13% versus 2%), and dyspnea (11% versus 0%).

8.5 Geriatric Use

The initial clinical trials of COREG CR in subjects with hypertension, heart failure, and left ventricular dysfunction following myocardial infarction did not include sufficient numbers of subjects aged 65 years or older to determine whether they respond differently from younger patients.

A randomized trial (n = 405) comparing subjects with mild to severe heart failure switched to COREG CR or maintained on immediate-release carvedilol included 220 subjects who were aged 65 years or older. In this elderly subgroup, the combined incidence of dizziness, hypotension, or syncope was 24% (18/75) in subjects switched from the highest dose of immediate-release carvedilol (25 mg twice daily) to the highest dose of COREG CR (80 mg once daily) compared with 11% (4/36) in subjects maintained on immediate-release carvedilol (25 mg twice daily). When switching from the higher doses of immediate-release carvedilol to COREG CR, a lower starting dose is recommended for elderly patients [see Dosage and Administration (2.5)].

The following information is available for trials with immediate-release carvedilol. Of the 765 subjects with heart failure randomized to carvedilol in U.S. clinical trials, 31% (235) were aged 65 years or older, and 7.3% (56) were aged 75 years or older. Of the 1,156 subjects randomized to carvedilol in a long-term, placebo-controlled trial ın severe heart failure, 47% (547) were aged 65 years or older, and 15% (174) were aged 75 years or older. Of 3,025 subjects receiving carvedilol in heart failure trials worldwide, 42% were aged 65 years or older. Of the 975 subjects with myocardial infarction randomized to carvedilol in the CAPRICORN trial, 48% (468) were aged 65 years or older, and 11% (111) were aged 75 years or older. Of the 2,065 hypertensive subjects in U.S. clinical trials of efficacy or safety who were treated with carvedilol, 21% (436) were aged 65 years or older. Of 3,722 subjects receiving immediate-release carvedilol in hypertension clinical trials conducted worldwide, 24% were aged 65 years or older.

With the exception of dizziness in hypertensive subjects (incidence 8.8% in the elderly versus 6% in younger subjects), no overall differences in the safety or effectiveness (see Figures 2 and 4) were observed between the older subjects and younger subjects in each of these populations. Similarly, other reported clinical experience has not identified differences in responses between the elderly and younger subjects, but greater sensitivity of some older individuals cannot be ruled out.

10 OVERDOSAGE

Overdosage may cause severe hypotension, bradycardia, cardiac insufficiency, cardiogenic shock, and cardiac arrest. Respiratory problems, bronchospasms, vomiting, lapses of consciousness, and generalized seizures may also occur.

The patient should be placed in a supine position and, where necessary, kept under observation and treated under intensive-care conditions. The following agents may be administered:

For excessive bradycardia: Atropine, 2 mg IV.

To support cardiovascular function: Glucagon, 5 to 10 mg IV rapidly over 30 seconds, followed by a continuous infusion of 5 mg per hour, sympathomimetics (dobutamine, isoprenaline, adrenaline) at doses according to body weight and effect.

If peripheral vasodilation dominates, it may be necessary to administer adrenaline or noradrenaline with continuous monitoring of circulatory conditions. For therapy-resistant bradycardia, pacemaker therapy should be performed. For bronchospasm, β-sympathomimetics (as aerosol or IV) or aminophylline IV should be given. In the event of seizures, slow IV injection of diazepam or clonazepam is recommended.

NOTE: In the event of severe intoxication where there are symptoms of shock, treatment with antidotes must be continued for a sufficiently long period of time consistent with the 7- to 10-hour half-life of carvedilol.

There is no experience of overdosage with COREG CR. Cases of overdosage with carvedilol alone or in combination with other drugs have been reported. Quantities ingested in some cases exceeded 1,000 milligrams. Symptoms experienced included low blood pressure and heart rate. Standard supportive treatment was provided and individuals recovered.

11 DESCRIPTION

Carvedilol phosphate is a nonselective β-adrenergic blocking agent with α1-blocking activity. It is (2RS)-1-(9H-Carbazol-4-yloxy)-3-[[2-(2-methoxyphenoxy)ethyl]amino]propan-2-ol phosphate salt (1:1) hemihydrate. It is a racemic mixture with the following structure:

Carvedilol phosphate is a white-to-almost white solid with a molecular weight of 513.5 (406.5 carvedilol free base) and a molecular formula of C24H26N2O4∙H3PO4∙1/2 H2O.

COREG CR is available for once-a-day administration as controlled-release oral capsules contaıning 10, 20, 40, or 80 mg carvedilol phosphate. COREG CR hard gelatin capsules are filled with carvedilol phosphate immediate-release and controlled-release microparticles that are drug-layered and then coated with methacrylic acid copolymers. Inactive ingredients include crospovidone, hydrogenated castor oil, hydrogenated vegetable oil, magnesium stearate, methacrylic acid copolymers, microcrystalline cellulose, and povidone.

12 CLINICAL PHARMACOLOGY

12.1 Mechanism of Action

Carvedilol is a racemic mixture in which nonselective β-adrenoreceptor blocking activity is present in the S(-) enantiomer and α1-adrenergic blocking activity is present in both R(+) and S(-) enantiomers at equal potency. Carvedilol has no intrinsic sympathomimetic activity.

12.2 Pharmacodynamics

Heart Failure and Left Ventricular Dysfunction following Myocardial Infarction

The basis for the beneficial effects of carvedilol in patients with heart failure and in patients with left ventricular dysfunction following an acute myocardial infarction is not known. The concentration-response relationship for β1-blockade following administration of COREG CR is equivalent (±20%) to immediate-release carvedilol tablets.

Hypertension

The mechanism by which β-blockade produces an antihypertensive effect has not been established.

β-adrenoreceptor blocking activity has been demonstrated in animal and human studies showing that carvedilol (1) reduces cardiac output in normal subjects, (2) reduces exercise- and/or isoproterenol-induced tachycardia, and (3) reduces reflex orthostatic tachycardia. Significant β-adrenoreceptor blocking effect is usually seen within 1 hour of drug administration.

α1-adrenoreceptor blocking activity has been demonstrated in human and animal studies, showing that carvedilol (1) attenuates the pressor effects of phenylephrine, (2) causes vasodilation, and (3) reduces peripheral vascular resistance. These effects contribute to the reduction of blood pressure and usually are seen within 30 minutes of drug administration.

Due to the α1-receptor blocking activity of carvedilol, blood pressure is lowered more in the standing than in the supine position, and symptoms of postural hypotension (1.8%), including rare instances of syncope, can occur. Following oral administration, when postural hypotension has occurred, it has been transient and is uncommon when immediate-release carvedilol is administered with food at the recommended starting dose and titration increments are closely followed [see Dosage and Administration (2)].

In a randomized, double-blind, placebo-controlled trial, the β1-blocking effect of COREG CR, as measured by heart rate response to submaximal bicycle ergometry, was shown to be equivalent to that observed with immediate-release carvedilol at steady state in adult subjects with essential hypertension.

In hypertensive subjects with normal renal function, therapeutic doses of carvedilol decreased renal vascular resistance with no change in glomerular filtration rate or renal plasma flow. Changes in excretion of sodium, potassium, uric acid, and phosphorus in hypertensive patients with normal renal function were similar after carvedilol and placebo.

Carvedilol has little effect on plasma catecholamines, plasma aldosterone, or electrolyte levels, but it does significantly reduce plasma renin activity when given for at least 4 weeks. It also increases levels of atrial natriuretic peptide.

12.3 Pharmacokinetics

Absorption

Carvedilol is rapidly and extensively absorbed following oral administration of immediate-release carvedilol tablets, with an absolute bioavailability of approximately 25% to 35% due to a significant degree of first-pass metabolism. COREG CR extended-release capsules have approximately 85% of the bioavailability of immediate-release carvedilol tablets. For corresponding dosages [see Dosage and Administration (2)], the exposure (AUC, Cmax, trough concentration) of carvedilol as COREG CR extended-release capsules is equivalent to those of immediate-release carvedilol tablets when both are administered with food. The absorption of carvedilol from COREG CR is slower and more prolonged compared with the immediate-release carvedilol tablet with peak concentrations achieved approximately 5 hours after administration. Plasma concentrations of carvedilol increase in a dose-proportional manner over the dosage range of COREG CR 10 to 80 mg. Within-subject and between-subject variabilıty for AUC and Cmax is similar for COREG CR and immediate-release carvedilol.

Effect of Food: Admınistration of COREG CR with a high-fat meal resulted in increases (~20%) in AUC and Cmax compared with COREG CR administered with a standard meal. Decreases in AUC (27%) and Cmax (43%) were observed when COREG CR was administered in the fasted state compared with administration after a standard meal. COREG CR should be taken with food.

In a trial with adult subjects, sprinkling the contents of the COREG CR capsule on applesauce did not appear to have a significant effect on overall exposure (AUC) compared with administration of the intact capsule following a standard meal, but did result in a decrease in Cmax (18%).

Distribution

Carvedilol is more than 98% bound to plasma proteins, primarily with albumin. The plasma-protein binding is independent of concentration over the therapeutic range. Carvedilol is a basic, lipophilic compound with a steady-state volume of distribution of approximately 115 L, indicating substantial distribution into extravascular tissues.

Metabolism and Excretion

Carvedilol is extensively metabolized. Following oral administration of radiolabelled carvedilol to healthy volunteers, carvedilol accounted for only about 7% of the total radioactivity in plasma as measured by AUC. Less than 2% of the dose was excreted unchanged in the urine. Carvedilol is metabolized primarily by aromatic ring oxidation and glucuronidation. The oxidative metabolites are further metabolized by conjugation via glucuronidation and sulfation. The metabolites of carvedilol are excreted primarily via the bile into the feces. Demethylation and hydroxylation at the phenol ring produce 3 active metabolites with β-receptor blocking activity. Based on preclinical studies, the 4'-hydroxyphenyl metabolite is approximately 13 times more potent than carvedilol for β-blockade.

Compared with carvedilol, the 3 active metabolites exhibit weak vasodilating activity. Plasma concentrations of the active metabolites are about one-tenth of those observed for carvedilol and have pharmacokinetics similar to the parent.

Carvedilol undergoes stereoselective first-pass metabolism with plasma levels of R(+)-carvedilol approximately 2 to 3 times higher than S(-)-carvedilol following oral administration of COREG C-R in healthy subjects. Apparent clearance is 90 L per h and 213 L per h for R(+)- and S(-)-carvedilol, respectively.

The primary P450 enzymes responsible for the metabolism of both R(+) and S(-)-carvedilol in human liver microsomes were CYP2D6 and CYP2C9 and to a lesser extent CYP3A4, 2C19, 1A2, and 2E1. CYP2D6 is thought to be the major enzyme in the 4'- and 5'-hydroxylation of carvedilol, with a potential contribution from 3A4. CYP2C9 is thought to be of primary importance in the O-methylation pathway of S(-)-carvedilol.

Carvedilol is subject to the effects of genetic polymorphism with poor metabolizers of debrisoquin (a marker for cytochrome P450 2D6) exhibiting 2- to 3-fold higher plasma concentrations of R(+)-carvedilol compared with extensive metabolizers. In contrast, plasma levels of S(-)-carvedilol are increased only about 20% to 25% in poor metabolizers, indicating this enantiomer is metabolized to a lesser extent by cytochrome P450 2D6 than R(+)-carvedilol. The pharmacokinetics of carvedilol do not appear to be different in poor metabolizers of S-mephenytoin (patients deficient in cytochrome P450 2C19).

12.4 Specific Populations

Heart Failure: Following administration of immediate-release carvedilol tablets, steady-state plasma concentrations of carvedilol and its enantiomers increased proportionally over the dose range in subjects with heart failure. Compared with healthy subjects, subjects with heart failure had increased mean AUC and Cmax values for carvedilol and its enantiomers, with up to 50% to 100% higher values observed in 6 subjects with NYHA class IV heart failure. The mean apparent terminal elimination half-life for carvedilol was similar to that observed in healthy subjects.

For corresponding dose levels [see Dosage and Administration (2)], the steady-state pharmacokinetics of carvedilol (AUC, Cmax, trough concentrations) observed after administration of COREG CR to subjects with chronic heart failure (mild, moderate, and severe) were similar to those observed after administration of immediate-release carvedilol tablets.

Hypertension: For corresponding dose levels [see Dosage and Administration (2)], the pharmacokinetics (AUC, Cmax, and trough concentrations) observed with administration of COREG CR were equivalent (±20%) to those observed with immediate-release carvedilol tablets following repeat dosing in subjects with essential hypertension.

Geriatric: Plasma levels of carvedilol average about 50% higher in the elderly compared with young subjects after administration of immediate-release carvedilol.

Hepatic Impairment: No trials have been performed with COREG CR in subjects with hepatic impairment. Compared with healthy subjects, subjects with severe liver impairment (cirrhosis) exhibit a 4- to 7-fold increase in carvedilol levels. Carvedilol is contraindicated in patients with severe liver impairment.

Renal Impairment: No trials have been performed with COREG CR in subjects with renal impairment. Although carvedilol is metabolized primarily by the liver, plasma concentrations of carvedilol have been reported to be increased in patients with renal impairment after dosing with immediate-release carvedilol. Based on mean AUC data, approximately 40% to 50% higher plasma concentrations of carvedilol were observed in subjects with hypertension and moderate to severe renal impairment compared with a control group of subjects with hypertension and normal renal function. However, the ranges of AUC values were similar for both groups. Changes in mean peak plasma levels were less pronounced, approximately 12% to 26% higher in subjects with impaired renal function.

Consistent with its high degree of plasma protein binding, carvedilol does not appear to be cleared significantly by hemodialysis.

12.5 Drug-Drug Interactions

Since carvedilol undergoes substantial oxidative metabolism, the metabolism and pharmacokinetics of carvedilol may be affected by induction or inhibition of cytochrome P450 enzymes.

The following drug interaction trials were performed with immediate-release carvedilol tablets.

Amiodarone: In a pharmacokinetic trial conducted in 106 Japanese subjects with heart failure, coadministration of small loading and maintenance doses of amiodarone with carvedilol resulted in at least a 2-fold increase in the steady-state trough concentrations of S(-)-carvedilol [see Drug Interactions (7.6)].

Cimetidine: In a pharmacokinetic trial conducted in 10 healthy male subjects, cimetidine (1,000 mg per day) increased the steady-state AUC of carvedilol by 30% with no change in Cmax [see Drug Interactions (7.5)].

Digoxin: Following concomitant administration of carvedilol (25 mg once daily) and digoxin (0.25 mg once daily) for 14 days, steady-state AUC and trough concentrations of digoxin were increased by 14% and 16%, respectively, in 12 subjects with hypertension [see Drug Interactions (7.4)].

Glyburide: In 12 healthy subjects, combined administration of carvedilol (25 mg once daily) and a single dose of glyburide did not result in a clinically relevant pharmacokinetic interaction for either compound.

Hydrochlorothiazide: A single oral dose of carvedilol 25 mg did not alter the pharmacokinetics of a single oral dose of hydrochlorothiazide 25 mg in 12 subjects with hypertension. Likewise, hydrochlorothiazide had no effect on the pharmacokinetics of carvedilol.

Rifampin: In a pharmacokinetic trial conducted in 8 healthy male subjects, rifampin (600 mg daily for 12 days) decreased the AUC and Cmax of carvedilol by about 70% [see Drug Interactions (7.5)].

Torsemide: In a trial of 12 healthy subjects, combined oral administration of carvedilol 25 mg once daily and torsemide 5 mg once daily for 5 days did not result in any significant differences in their pharmacokinetics compared with administration of the drugs alone.

Warfarin: Carvedilol (12.5 mg twice daily) did not have an effect on the steady-state prothrombin time ratios and did not alter the pharmacokinetics of R(+)- and S(-)-warfarin following concomitant administration with warfarin in 9 healthy volunteers.

13 NONCLINICAL TOXICOLOGY

13.1 Carcinogenesis, Mutagenesis, Impairment of Fertility

In 2-year studies conducted in rats given carvedilol at doses up to 75 mg per kg per day (12 times the MRHD as mg per m2) or in mice given up to 200 mg per kg per day (16 times the MRHD as mg per m^2), carvedilol had no carcinogenic effect.

Carvedilol was negative when tested in a battery of genotoxicity assays, including the Ames and the CHO/HGPRT assays for mutagenicity and the in vitro hamster micronucleus and in vivo human lymphocyte cell tests for clastogenicity.

In a combined fertility/developmental/post-natal toxicity study, rats were given carvedilol (12, 60, 300 mg per kg per day) orally by gavage for 2 weeks before mating and through mating, gestation, and weaning for females and for 62 days prior to and through mating for males. At a dosage of 300 mg per kg per day (greater than or equal to 50 times the MRHD as mg per m^2) carvedilol was toxic to adult rats (sedation, reduced weight gain) and was associated with a reduced number of successful matings, prolonged mating time, fewer corpora lutea and implants per dam, fewer live pups per litter, and delays in physical growth/development. The no-effect level for overt toxicity and impairment of fertility was 60 mg per kg per day (10 times the MRHD as mg per m^2).

14 CLINICAL STUDIES

Support for the use of COREG CR extended-release capsules for the treatment of mild-to-severe heart failure and for patients with left ventricular dysfunction following myocardial infarction is based on the equivalence of pharmacokinetic and pharmacodynamic (β1-blockade) parameters between COREG CR and immediate-release carvedilol [see Clinical Pharmacology (12.2, 12.3)].

The clinical trials performed with immediate-release carvedilol in heart failure and left ventricular dysfunction following myocardial infarction are presented below.

14.1 Heart Failure

A total of 6,975 subjects with mild-to-severe heart failure were evaluated in placebo-controlled and active-controlled trials of immediate-release carvedilol.

Mild-to-Moderate Heart Failure

Carvedilol was studied in 5 multicenter, placebo-controlled trials, and in 1 active-controlled trial (COMET trial) involving subjects with mild-to-moderate heart failure.

Four U.S. multicenter, double-blind, placebo-controlled trials enrolled 1,094 subjects (696 randomized to carvedilol) with NYHA class II-III heart failure and ejection fraction less than or equal to 0.35. The vast majority were on digitalis, diuretics, and an ACE inhibitor at trial entry. Subjects were assigned to the trials based upon exercise ability. An Australia-New Zealand double-blind, placebo-controlled trial enrolled 415 subjects (half randomized to immediate-release carvedilol) with less severe heart failure. All protocols excluded subjects expected to undergo cardiac transplantation during the 7.5 to 15 months of double-blind follow-up. All randomized subjects had tolerated a 2-week course on immediate-release carvedilol 6.25 mg twice daily.

In each trial, there was a primary end point, either progression of heart failure (1 U.S. trial) or exercise tolerance (2 U.S. trials meeting enrollment goals and the Australia-New Zealand trial). There were many secondary end points specified in these trials, including NYHA classification, patient and physician global assessments, and cardiovascular hospitalization. Other analyses not prospectively planned included the sum of deaths and total cardiovascular hospitalizations. In situations where the primary end points of a trial do not show a significant benefit of treatment, assignment of significance values to the other results is complex, and such values need to be interpreted cautiously.

The results of the U.S. and Australia-New Zealand trials were as follows:

Slowing Progression of Heart Failure: One U.S. multicenter trial (366 subjects) had as its primary end point the sum of cardiovascular mortality, cardiovascular hospitalization, and sustained increase in heart failure medications. Heart failure progression was reduced, during an average follow-up of 7 months, by 48% (P = 0.008).

In the Australia-New Zealand trial, death and total hospitalizations were reduced by about 25% over 18 to 24 months. In the 3 largest U.S. trials, death and total hospitalizations were reduced by 19%, 39%, and 49%, nominally statistically significant in the last 2 trials. The Australia-New Zealand results were statistically borderline.

Functional Measures: None of the multicenter trials had NYHA classification as a primary end point, but all such trials had it as a secondary end point. There was at least a trend toward improvement in NYHA class in all trials. Exercise tolerance was the primary end point in 3 trials, in none was a statistically significant effect found.

Subjective Measures: Health-related quality of life, as measured with a standard questionnaire (a primary end point in 1 trial), was unaffected by carvedilol. However, patients' and investigators' global assessments showed significant improvement in most trials

Mortality: Death was not a pre-specified end point in any trial but was analyzed in all trials. Overall, in these 4 U.S. trials, mortality was reduced, nominally significantly so in 2 trials.

The COMET Trial

In this double-blind trial, 3,029 subjects with NYHA class II-IV heart failure (left ventricular ejection fraction less than or equal to 35%) were randomized to receive either carvedilol (target dose: 25 mg twice daily) or immediate-release metoprolol tartrate (target dose.. 50 mg twice daily). The mean age of the subjects was approximately 62 years, 80% were males, and the mean left ventricular ejection fraction at baseline was 26%. Approximately 96% of the subjects had NYHA class II or III heart failure. Concomitant treatment included diuretics (99%), ACE inhibitors (91%), digitalis (59%), aldosterone antagonists (11%), and "statin" lipid-lowering agents (21%). The mean duration of follow-up was 4.8 years. The mean dose of carvedilol was 42 mg per day.

The trial had 2 primary end points: all-cause mortality and the composite of death plus hospitalization for any reason. The results of COMET are presented in Table 5 below. All-cause mortality carried most of the statistical weight and was the primary determinant of the trial size. All-cause mortality was 34% in the subjects treated with carvedilol and was 40% in the immediate-release metoprolol group (P = 0.0017, hazard ratio = 0.83, 95% CI: 0.74 to 0.93). The effect on mortality was primarily due to a reduction in cardiovascular death. The difference between the 2 groups with respect to the composite end point was not significant (P = 0.122). The estimated mean survival was 8.0 years with carvedilol and 6.6 years with immediate-release metoprolol.

Table 5. Results of COMET
End Point | Carvedilol n = 1,511 | Metoprolol n = 1,518 | Hazard Ratio | (95% CI)
All-cause mortality | 34% | 40% | 0.83 | 0.74 - 0.93
Mortality + all hospitalization | 74% | 76% | 0.94 | 0.86 - 1.02
Cardiovascular death | 30% | 35% | 0.80 | 0.70 - 0.90
Sudden death | 14% | 17% | 0.81 | 0.68 - 0.97
Death due to circulatory failure | 11% | 13% | 0.83 | 0.67 - 1.02
Death due to stroke | 0.9% | 2.5% | 0.33 | 0.18 - 0.62

It is not known whether this formulation of metoprolol at any dose or this low dose of metoprolol in any formulation has any effect on survival or hospitalization in patients with heart failure. Thus, this trial extends the time over which carvedilol manifests benefits on survival in heart failure, but it is not evidence that carvedilol improves outcome over the formulation of metoprolol (TOPROL-XL) with benefits in heart failure.

Severe Heart Failure (COPERNICUS)

In a double-blind trial, 2,289 subjects with heart failure at rest or with minimal exertion and left ventricular ejection fraction less than 25% (mean 20%), despite digitalis (66%), diuretics (99%), and ACE inhibitors (89%), were randomized to placebo or carvedilol. Carvedilol was titrated from a starting dose of 3.125 mg twice daily to the maximum tolerated dose or up to 25 mg twice daily over a mınimum of 6 weeks. Most subjects achieved the target dose of 25 mg. The trial was conducted in Eastern and Western Europe, the United States, Israel, and Canada. Similar numbers of subjects per group (about 100) withdrew during the titration period.

The primary end point of the trial was all-cause mortality, but cause-specific mortality and the risk of death or hospitalization (total, cardiovascular [CV], or heart failure [HF]) were also examined. The developing trial data were followed by a data monitoring committee, and mortality analyses were adjusted for these multiple looks. The trial was stopped after a median follow-up of 10 months because of an observed 35% reduction in mortality (from 19.7% per patient-year on placebo to 12.8% on carvedilol: hazard ratio 0.65, 95% CI: 0.52 to 0.81, P = 0.0014, adjusted) (see Figure 1). The results of COPERNICUS are shown in Table 6.

Table 6. Results of COPERNICUS Trial in Subjects with Severe Heart Failure
End Point | Placebo (n = 1,133) | Carvedilol (n = 1,156) | Hazard Ratio (95% CI) | % Reduction | Nominal P value
Mortality | 190 | 130 | 0.65 (0.52 - 0.81) | 35 | 0.00013
Mortality + all hospitalization | 507 | 425 | 0.76 (0.67 - 0.87) | 24 | 0.00004
Mortality + CV hospitalization | 395 | 314 | 0.73 (0.63 - 0.84) | 27 | 0.00002
Mortality + HF hospitalization | 357 | 271 | 0.69 (0.59 - 0.81) | 31 | 0.000004
Cardiovascular = CV; Heart failure = HF.

Figure 1. Survival Analysis for COPERNICUS (Intent-to-Treat)

The effect on mortality was principally the result of a reduction in the rate of sudden death among subjects without worsening heart failure.

Patients' global assessments, in which carvedilol-treated subjects were compared with placebo, were based on pre-specified, periodic patient self-assessments regarding whether clinical status post-treatment showed improvement, worsening, or no change compared with baseline. Subjects treated with carvedilol showed significant improvements in global assessments compared with those treated with placebo in COPERNICUS.

The protocol also specified that hospitalizations would be assessed. Fewer subjects on immediate-release carvedilol than on placebo were hospitalized for any reason (372 versus 432, P=0.0029), for cardiovascular reasons (246 versus 314, P=0.0003), or for worsening heart failure (198 versus 268, P = 0.0001).

Immediate-release carvedilol had a consistent and beneficial effect on all-cause mortality as well as the combined end points of all-cause mortality plus hospitalization (total, CV, or for heart failure) in the overall trial population and in all subgroups examined, including men and women, elderly and non-elderly, blacks and non-blacks, and diabetics and non-diabetics (see Figure 2).

Figure 2. Effects on Mortality for Subgroups in COPERNICUS

Although the clinical trials used twice-daily dosing, clinical pharmacologic and pharmacokinetic data provide a reasonable basis for concluding that once-daily dosing with COREG CR should be adequate in the treatment of heart failure.

14.2 Left Ventricular Dysfunction following Myocardial Infarction

CAPRICORN was a double-blind trial comparing carvedilol and placebo in 1,959 subjects with a recent myocardial infarction (within 21 days) and left ventricular ejection fraction of less than or equal to 40%, with (47%) or without symptoms of heart failure. Subjects given carvedilol received 6.25 mg twice daily, titrated as tolerated to 25 mg twice daily. Subjects had to have a systolic blood pressure greater than 90 mm Hg, a sitting heart rate greater than 60 beats per minute, and no contraindication to β-blocker use. Treatment of the index infarction included aspirin (85%), IV or oral β-blockers (37%), nitrates (73%), heparin (64%), thrombolytics (40%), and acute angioplasty (12%). Background treatment included ACE inhibitors or angiotensin-receptor blockers (97%), anticoagulants (20%), lipid-lowering agents (23%), and diuretics (34%). Baseline population characteristics included an average age of 63 years, 74% male, 95% Caucasian, mean blood pressure 121/74 mm Hg, 22% with diabetes, and 54% with a history of hypertension. Mean dosage achieved of carvedilol was 20 mg twice daily, mean duration of follow-up was 15 months.

All-cause mortality was 15% in the placebo group and 12% in the carvedilol group, indicating a 23% risk reduction in subjects treated with carvedilol (95% CI: 2% to 40%, P = 0.03), as shown in Figure 3. The effects on mortality in various subgroups are shown in Figure 4. Nearly all deaths were cardiovascular (which were reduced by 25% by carvedilol), and most of these deaths were sudden or related to pump failure (both types of death were reduced by carvedilol). Another trial end point, total mortality and all-cause hospitalization, did not show a significant improvement.

There was also a significant 40% reduction in fatal or non-fatal myocardial infarction observed in the group treated with carvedilol (95% CI: 11% to 60%, P = 0.01). A similar reduction in the risk of myocardial infarction was also observed in a meta-analysis of placebo-controlled trials of carvedilol in heart failure.

Figure 3. Survival Analysis for CAPRICORN (Intent-to-Treat)

Figure 4. Effects on Mortality for Subgroups in CAPRICORN

Although the clinical trials used twice-daily dosing, clinical pharmacologic and pharmacokinetic data provide a reasonable basis for concluding that once-daily dosing with COREG CR should be adequate in the treatment of left ventricular dysfunction following myocardial infarction.

14.3 Hypertension

A double-blind, randomized, placebo-controlled, 8-week trial evaluated the blood pressure-lowering effects of COREG CR 20 mg, 40 mg, and 80 mg once daily in 338 subjects with essential hypertension (sitting diastolic blood pressure [DBP] greater than or equal to 90 and less than or equal to 109 mm Hg). Of 337 evaluable subjects, a total of 273 subjects (81%) completed the trial. Of the 64 (19%) subjects withdrawn from the trial, 10 (3%) were due to adverse events, 10 (3%) were due to lack of efficacy; the remaining 44 (13%) withdrew for other reasons. The mean age of the subjects was approximately 53 years, 66% were male, and the mean sıtting systolic blood pressure (SBP) and DBP at baseline were 150 mm Hg and 99 mm Hg, respectively. Dose titration occurred at 2-week intervals.

Statistically significant reductions in blood pressure as measured by 24-hour ambulatory blood pressure monitoring (ABPM) were observed with each dose of COREG CR compared with placebo. Placebo-subtracted mean changes from baseline in mean SBP/DBP were -6.1/-4.0 mm Hg, -9.4/-7.6 mm Hg, and 11.8/-9.2 mm Hg for COREG CR 20 mg, 40 mg, and 80 mg, respectively. Placebo-subtracted mean changes from baseline in mean trough (average of hours 20 to 24) SBP/DBP were -3.3/-2.8 mm Hg, 4.9/-5.2 mm Hg , and -8.4/-7.4 mm Hg for COREG CR 20 mg, 40 mg, and 80 mg, respectively. The placebo-corrected trough-to-peak (3 to 7 h) ratio was approximately 0.6 for COREG CR 80 mg. In this trial, assessments of 24-hour ABPM monitoring demonstrated statistically signif cant blood pressure reductions with COREG CR throughout the dosing period (Figure 5).

Figure 5. Changes from Baseline in Systolic Blood Pressure and Diastolic Blood Pressure Measured by 24-Hour ABPM

Immediate-release carvedilol was studied in 2 placebo-controlled trials that utilized twice-daily dosing at total daily doses of 12.5 to 50 mg. In these and other trials, the starting dose did not exceed 12.5 mg. At 50 mg per day, COREG reduced sittıng trough (12-hour) blood pressure by about 9/5.5 mm Hg, at 25 mg per day the effect was about 7.5/3.5 mm Hg. Comparisons of trough-to-peak blood pressure showed a trough-to-peak ratio for blood pressure response of about 65%. Heart rate fell by about 7.5 beats per minute at 50 mg per day. In general, as is true for other β-blockers, responses were smaller in black than non-black subjects. There were no age- or gender-related differences in response. The dose-related blood pressure response was accompanied by a dose-related increase in adverse effects [see Adverse Reactions (6)].

14.4 Hypertension with Type 2 Diabetes Mellitus

In a double-blind trial (GEMINI), carvedilol, added to an ACE inhibitor or angiotensin receptor blocker, was evaluated in a population with mild-to-moderate hypertension and well-controlled type 2 diabetes mellitus. The mean HbA1c at baseline was 7.2%. COREG was titrated to a mean dose of 17.5 mg twice daily and maintained for 5 months. COREG had no adverse effect on glycemic control, based on HbA1c measurements (mean change from baseline of 0.02%, 95% CI: -0.06 to 0.10, P = NS) [see Warnings and Precautions (5.6)].

16 HOW SUPPLIED/STORAGE AND HANDLING

The hard gelatin capsules are available in the following strengths:

- 10 mg - white and green capsule shell printed with ' GSLGK" and ' 10 mg"
- 20 mg - white and yellow capsule shell printed with ' GSMHV" and ' 20 mg"
- 40 mg - yellow and green capsule shell printed with "GSETX" and "40 mg"
- 80 mg - white capsule shell printed with ' GSF1L" and ' 80 mg"
- 10 mg bottles of 30: NDC 80725-383-13
- 20 mg bottles of 30: NDC 80725-385-13
- 40 mg bottles of 30: NDC 80725-387-13
- 80 mg bottles of 30: NDC 80725-388-13

STORAGE AND HANDLING

Store at 25°C (77°F); excursions 15° to 30°C (59° to 86°F). Dispense in a tight, light-resistant container.

17 PATIENT COUNSELING INFORMATION

Advise the patient to read the FDA-approved patient labeling (Patient Information).

Patients taking COREG CR should be advised of the following:

- Patients should not interrupt or discontinue using COREG CR without a physıcian's advice.
- Patients with heart failure should consult their physician if they experience signs or symptoms of worsening heart failure such as weight gain or increasing shortness of breath.
- Patients may experience a drop in blood pressure when standing, resulting in dizziness and, rarely, fainting. Patients should sit or lie down when these symptoms of lowered blood pressure occur.
- If experiencing dizziness or fatigue, patients should avoid driving or hazardous tasks.
- Patients should consult a physician if they experience dizziness or faintness, in case the dosage should be adjusted.
- Patients should not crush or chew COREG CR.
- Patients should take COREG CR with food.
- Inform patients or caregivers that there is a risk of hypoglycemia when Coreg is given to patients who are fasting or who are vomiting. Instruct patients or caregivers how to monitor for signs of hypoglycemia [see Warnings and Precautions (5.6)].
- Contact lens wearers may experience decreased lacrimation.

COREG CR and COREG are trademarks used under license by Waylis Therapeutics LLC.

The other brand listed is a trademark owned by or licensed to its owner and is not owned by or licensed to Waylis Therapeutics LLC. The maker of this brand is not affiliated with and does not endorse Waylis Therapeutics LLC or its products.

Manufactured for:
Waylis Therapeutics LLC
Rahway, NJ 07065

PATIENT INFORMATION COREG CR (Co-REG) (carvedilol phosphate) Extended-release Capsules

Read the Patient Information that comes with COREG CR before you start taking it and each time you get a refill. There may be new information. This information does not take the place of talking with your doctor about your medical condition or your treatment. If you have any questions about COREG CR, ask your doctor or pharmacist.

What is the most important information I should know about COREG CR?

It is important for you to take your medicine every day as directed by your doctor. If you stop taking COREG CR suddenly, you could have chest pain and a heart attack. If your doctor decides that you should stop taking COREG CR, your doctor may slowly lower your dose over time before stopping it completely.

What is COREG CR?

COREG CR is a prescription medicine that belongs to a group of medicines called ' beta-blockers". COREG CR is used, often with other medicines, for the following conditions:

- to treat patients with certain types of heart failure
- to treat patients who had a heart attack that worsened how well the heart pumps
- to treat patients with high blood pressure (hypertension)

COREG CR is not approved for use in children under 18 years of age.

Who should not take COREG CR?

Do not take COREG CR if you:

- have severe heart failure and require certain intravenous medicines that help support circulation.
- have asthma or other breathing problems.
- have a slow heartbeat or certain conditions that cause your heart to skip a beat (irregular heartbeat).
- have liver problems.
- are allergic to any of the ingredients in COREG CR. See "What are the ingredients in COREG CR?"

What should I tell my doctor before taking COREG CR?

Tell your doctor about all of your medical conditions, including if you:

- have asthma or other lung problems (such as bronchitis or emphysema).
- have problems with blood flow in your feet and legs (peripheral vascular disease). COREG CR can make some of your symptoms worse.
- have diabetes.
- have thyroid problems.
- have a condition called pheochromocytoma.
- have had severe allergic reactions.
- are scheduled for surgery and will be given anesthetic agents.
- are scheduled for cataract surgery and have taken or are currently taking COREG CR.
- are pregnant or trying to become pregnant. It is not known if COREG CR is safe for your unborn baby. You and your doctor should talk about the best way to control your high blood pressure during pregnancy.
- are breastfeeding. It is not known if COREG CR passes into your breast milk. Talk with your doctor about the best way to feed your baby if you are taking COREG CR.

Tell your doctor about all of the medicines you take including prescription and over-the-counter medicines, vitamins, and herbal supplements. COREG CR and certain other medicines can affect each other and cause serious side effects. COREG CR may affect the way other medicines work. Also, other medicines may affect how well COREG CR works.

Know the medicines you take. Keep a list of your medicines and show it to your doctor and pharmacist before you start a new medicine.

How should I take COREG CR?

- Take COREG CR exactly as prescribed. Take COREG CR one time each day with food. It is important that you take COREG CR only one time each day. To lessen possible side effects, your doctor might begin with a low dose and then slowly increase the dose.
- Swallow COREG CR capsules whole. Do not chew or crush COREG CR capsules.
- If you have trouble swallowing COREG CR whole:
  - The capsule may be carefully opened and the beads sprinkled over a spoonful of applesauce which should be eaten right away. The applesauce should not be warm.
  - Do not sprinkle beads on foods other than applesauce.
- Do not stop taking COREG CR and do not change the amount of COREG CR you take without talking to your doctor.
- If you miss a dose of COREG CR, take your dose as soon as you remember, unless it is time to take your next dose. Take your next dose at the usual time. Do not take 2 doses at the same time.
- If you take too much COREG CR, call your doctor or poison control center right away.

What should I avoıd whıle takıng COREG CR?

COREG CR can cause you to feel dizzy, tired, or faint. Do not drive a car, use machinery, or do anything that needs you to be alert if you have these symptoms.

What are possible side effects of COREG CR?

Serious side effects of COREG CR include:

- chest pain and heart attack if you suddenly stop taking COREG CR. See "What is the most important information I should know about COREG CR?"
- slow heart beat.
- low blood pressure (which may cause dizziness or fainting when you stand up). If these happen, sit or lie down, and tell your doctor right away.
- worsening heart failure. Tell your doctor right away if you have signs and symptoms that your heart failure may be worse, such as weight gain or increased shortness of breath.
- changes in your blood sugar. If you have diabetes, tell your doctor if you have any changes in your blood sugar levels.
- masking (hiding) the symptoms of low blood sugar, especially a fast heartbeat.
- new or worsening symptoms of peripheral vascular disease.
  - leg pain that happens when you walk, but goes away when you rest
  - no feeling (numbness) in your legs or feet while you are resting
  - cold legs or feet
- masking the symptoms of hyperthyroidism (overactive thyroid), such as a fast heartbeat.
- worsening of severe allergic reactions. Medicines to treat a severe allergic reaction may not work as well while you are taking COREG CR.
- rare but serious allergic reactions (including hives or swelling of the face, lips, tongue, and/or throat that may cause difficulty in breathing or swallowing) have happened in patients who were on COREG or COREG CR. These reactions can be life-threatening. In some cases, these reactions happened in patients who had been on COREG before taking COREG CR.

Common side effects of COREG CR include shortness of breath, weight gain, diarrhea, and tiredness. If you wear contact lenses, you may have fewer tears or dry eyes that can become bothersome.

Call your doctor if you have any side effects that bother you or don't go away.

Call your doctor for medical advice about side effects. You may report side effects to FDA at 1-800-FDA-1088.

How should I store COREG CR?

Store COREG CR at less than 86°F (30°C).

Safely throw away COREG CR that is out of date or no longer needed.

Keep COREG CR and all medicines out of the reach of children.

General information about COREG CR

Medicines are sometimes prescribed for conditions other than those described in patient information leaflets. Do not use COREG CR for a condition for which it was not prescribed. Do not give COREG CR to other people, even if they have the same symptoms you have. It may harm them.

This leaflet summarizes the most important information about COREG CR. If you would like more information, talk with your doctor. You can ask your doctor or pharmacist for information about COREG CR that is written for healthcare professionals.

What are the ingredients in COREG CR?

Active ingredient: carvedilol phosphate

Inactive ingredients: crospovidone, hydrogenated castor oil, hydrogenated vegetable oil, magnesium stearate, methacrylic acid copolymers, microcrystalline cellulose, and povidone.

COREG CR capsules come in the following strengths: 10 mg, 20 mg, 40 mg, 80 mg.

What is high blood pressure (hypertension)?

Blood pressure is the force of blood in your blood vessels when your heart beats and when your heart rests. You have high blood pressure when the force is too much. High blood pressure makes the heart work harder to pump blood through the body and causes damage to blood vessels. COREG CR can help your blood vessels relax so your blood pressure is lower. Medicines that lower blood pressure may lower your chance of having a stroke or heart attack.

COREG CR and COREG are trademarks used under license by Waylis Therapeutics LLC.

Manufactured for:
Waylis Therapeutics LLC
Rahway, NJ 07065

Rev. 10/2024

PRINCIPAL DISPLAY PANEL - 10 mg Capsule Bottle Label

10 mg

Waylis
THERAPEUTICS

NDC 80725-383-13

ONCE-A-DAY
DOSING

COREG CR
(carvedilol phosphate)
Extended-release Capsules

30 Capsules
Rx only

PRINCIPAL DISPLAY PANEL - 20 mg Capsule Bottle Label

20 mg

Waylis
THERAPEUTICS

NDC 80725-385-13

ONCE-A-DAY
DOSING

COREG CR
(carvedilol phosphate)
Extended-release Capsules

30 Capsules
Rx only

PRINCIPAL DISPLAY PANEL - 40 mg Capsule Bottle Label

40 mg

Waylis
THERAPEUTICS

NDC 80725-387-13

ONCE-A-DAY
DOSING

COREG CR
(carvedilol phosphate)
Extended-release Capsules

30 Capsules
Rx only

PRINCIPAL DISPLAY PANEL - 80 mg Capsule Bottle Label

80 mg

Waylis
THERAPEUTICS

NDC 80725-388-13

ONCE-A-DAY
DOSING

COREG CR
(carvedilol phosphate)
Extended-release Capsules

30 Capsules
Rx only